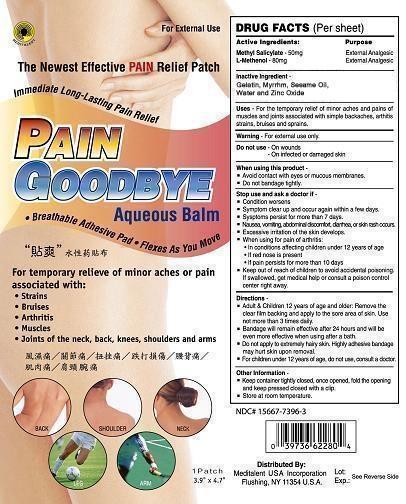 DRUG LABEL: PAIN GOODBYE AQUEOUS PATCH
NDC: 15667-7396 | Form: PATCH
Manufacturer: Austin Biotechnology Inc
Category: otc | Type: HUMAN OTC DRUG LABEL
Date: 20131010

ACTIVE INGREDIENTS: METHYL SALICYLATE 50 mg/1000 mg; 2-(L-MENTHOXY)ETHANOL 80 mg/1000 mg
INACTIVE INGREDIENTS: GELATIN; MYRRH; SESAME OIL; WATER; ZINC OXIDE

PAIN GOODBYE AQUEOUS BALM PATCH

ACTIVE INGREDIENTS

Methyl Salicylate 50 mg

L-Methenol 80 mg

PURPOSE

Methyl Salucylate External Analgesic

L-Methenol External Analgesic

USES

Uses for the temporary relief of minor aches, and points of muscles and joints associated with simple backache, arthritis, strains, bruises and sprains.

WARNINGS

For External Use Only. Do not use on wounds, on infected or damaged skin.

Stop use and ask a doctor if

Keep out of reach of children to avoid accidental poisoning. If swallowed, get medical help or consult a poison control center right away.

Stop use and ask a doctor if

Condition worsens.

Symptom clears up and occurs again within a few days.

Symptom persists for more than 7 days.

Nausea, vomitting, abdominal discomfort, diarrhea, or skin rash occurs.

Excessive irritation of the skin develops.

Stop use and ask a doctor if

Avoid contact with eyes or mucous membranes.

Do not bandage tightly.

When using for pain of arthritis:

In conditions affecting children under 12 years of age

If red nose is present

If pain persists for more than 10 days

WARNINGS

For children under 12 years of age, do not use, consult a doctor.

Directions

Adult and children 12 years of age and older; Remove the clear film backing and apply to the sore area of skin. Use not than 3 times daily.

Bandage will remain effective after 24 hours and will be even more effective when using after a bath.

Do not apply to extremely hairy skin. Highly adhesive bandage may hurt skin upon removal.

Other Information:

Keep container tightly closed. Once opened, fold the opening and keep pressed. Close with a clip.

Store at room temperature.

INACTIVE INGREDIENTS

Gelatin, Myrrhm, Sesame Oil, Water and Zinc Oxide